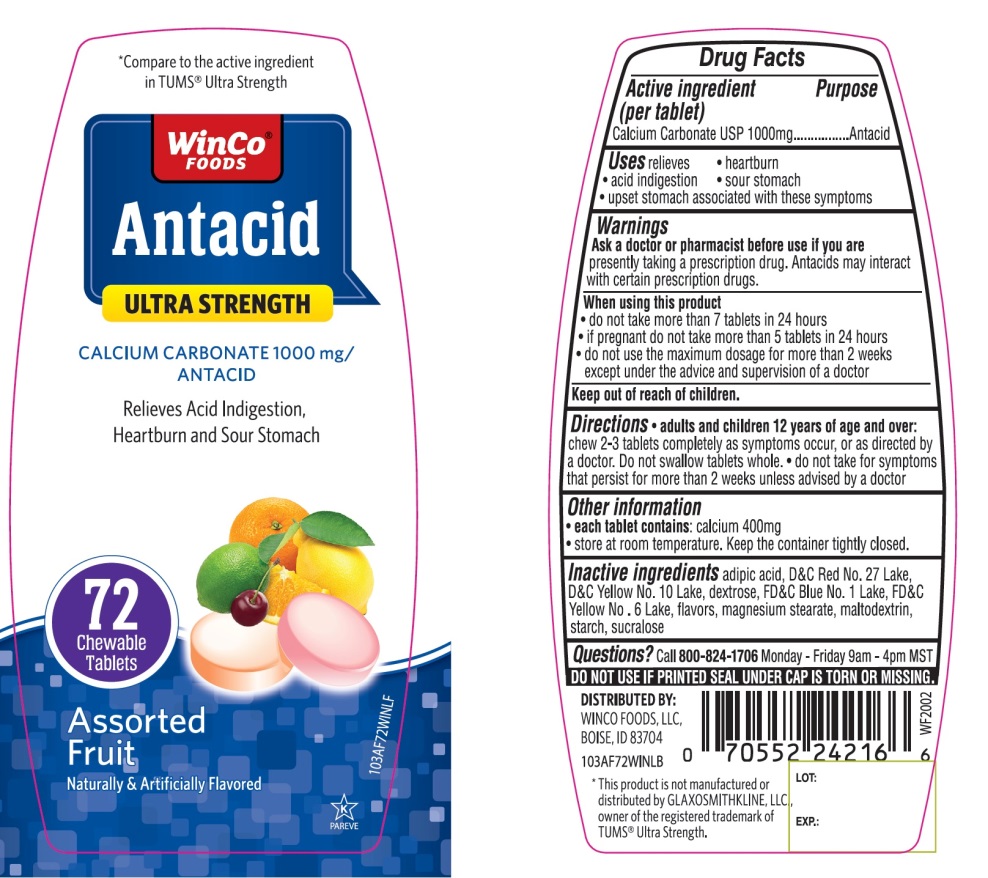 DRUG LABEL: WinCo FOODS Antacid

NDC: 67091-365 | Form: TABLET, CHEWABLE
Manufacturer: WINCO FOODS, LLC
Category: otc | Type: HUMAN OTC DRUG LABEL
Date: 20251202

ACTIVE INGREDIENTS: CALCIUM CARBONATE 1000 mg/1 1
INACTIVE INGREDIENTS: ADIPIC ACID; D&C RED NO. 27; D&C YELLOW NO. 10; DEXTROSE, UNSPECIFIED FORM; FD&C BLUE NO. 1; FD&C YELLOW NO. 6; MAGNESIUM STEARATE; MALTODEXTRIN; STARCH, CORN; SUCRALOSE

WinCo®FOODS Ultra Strength Antacid Calcium Carbonate Chewable Tablets

Active ingredient (per tablet)

Calcium Carbonate USP 1000mg

Purpose

Antacid

Uses

relieves

- heartburn
- acid indigestion
- sour stomach
- upset stomach associated with these symptoms

Warnings

Ask a doctor or pharmacist before use if you arepresently taking a prescription drug. Antacids may interact with certain prescription drugs.

When using this product

- do not take more than 7 tablets in 24 hours
- if pregnant do not take more than 5 tablets in 24 hours
- do not use the maximum dosage for more than 2 weeks except under the advice and supervision of a doctor.

Directions

- adults and children 12 years of age and over:chew 2-3 tablets as symptoms occur, or as directed by a doctor
- do not take for symptoms that persist for more than 2 weeks unless advised by a doctor

Other information

- each tablet contains:calcium 400mg
- Store at room temperature. Keep the container tightly closed.

Inactive ingredients

adipic acid, D&C Red No. 27, D&C Yellow No. 10, dextrose, FD&C Blue No. 1, FD&C Yellow No. 6, flavors, magnesium stearate, maltodextrin, starch, sucralose.

Questions?

Call 1-800-824-1706 Monday – Friday 9am – 4pm MST

SAFETY SEALED: DO NOT USE IF PRINTED SEAL UNDER CAP IS TORN OR MISSING

Package/Label Principal Display Panel

NDC 67091-365-72

*Compare to the active ingredient in TUMS®Ultra Strength

Antacid

ULTRA STRENGTH

CALCIUM CARBONATE 1000 mg/ANTACID

Assorted Fruit Flavor

Naturally and Artificially Flavored

Relieves of Acid Indigestion, Heartburn and Sour Stomach

72 Chewable Tablets

K PAREVE

GLUTEN- FREE

DISTRIBUTED BY:

WINCO FOODS, LLC,

BOISE, ID 83704

*This product is not manufactured or distributed by GLAXOSMITHKLINE LLC, owner of the registered trademark, TUMS® Ultra Strength.